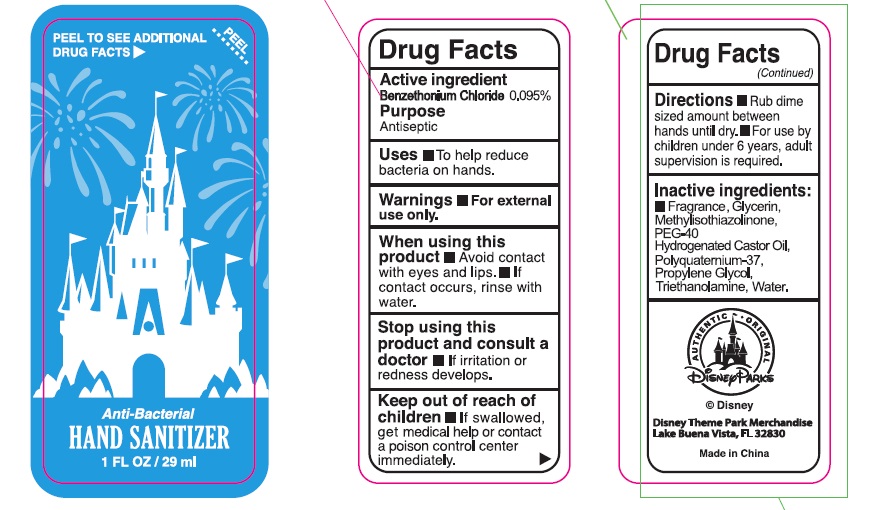 DRUG LABEL: Hand Sanitizer
NDC: 72707-001 | Form: GEL
Manufacturer: DISNEY DESTINATIONS,LLC
Category: otc | Type: HUMAN OTC DRUG LABEL
Date: 20181127

ACTIVE INGREDIENTS: BENZETHONIUM CHLORIDE 0.095 g/100 mL
INACTIVE INGREDIENTS: PROPYLENE GLYCOL; GLYCERIN; METHYLISOTHIAZOLINONE; POLYQUATERNIUM 37 (200 MPA.S); WATER; TROLAMINE; POLYOXYL 40 HYDROGENATED CASTOR OIL

Active Ingredient:
Benzethonium Chloride 0.095%

Purpose

Antiseptic

STOP USE

Stop using this product and consult a doctor if irritation or redness develops.

Keep out of reach of children. If swallowed, get medical help or contact a poison control center immediately.

Directions

- Rub dime sized amount between hands until dry.
- For use by children under 6 years, adult supervision is required.

Inactive Ingredients

Fragrance, Glycerin, Methylisothiazolinone, PEG-40 Hydrogenated Castor Oil, Polyquatemium-37, Propylene Glycol, Triethanolamine, Water,

Uses

To help reduce bacteria on hands.

Warnings:

For external use only.

When using this product,

- Avoid contact with eyes and lips.
- If contact occurs, rinse with water.